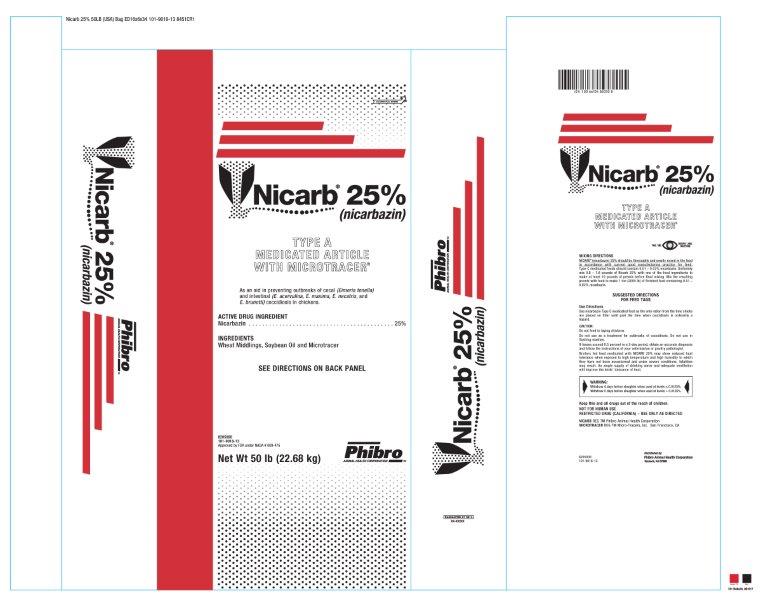 DRUG LABEL: Nicarb
NDC: 66104-8200 | Form: POWDER
Manufacturer: Phibro Animal Health
Category: animal | Type: OTC TYPE A MEDICATED ARTICLE ANIMAL DRUG LABEL
Date: 20231106

ACTIVE INGREDIENTS: NICARBAZIN 113.4 g/0.45 kg
INACTIVE INGREDIENTS: SOYBEAN OIL; WHEAT MIDDLINGS

Nicarb® 25%
(Nicarbazin)
TYPE A MEDICATED ARTICLE WITH MICROTRACER®

INDICATIONS AND USAGE

As an aid in preventing outbreaks of cecal (Eimeria tenella) and intestinal (E. acervulina, E. maxima, E. necatrix,and E. brunetti) coccidiosis in chickens.

ACTIVE DRUG INGREDIENT

Nicarbazin . . . . . . . . . . . . . . . . . . . . . . . . . . . . . . . . . . . . . . . . . . . 25%

INGREDIENTS

Wheat Middlings, Soybean Oil and Microtracer

MIXING DIRECTIONS

NICARB (nicarbazin) 25% should be thoroughly and evenly mixed in the feed in accordance with current good manufacturing practice for feed. Type C medicated feeds should contain 0.01 – 0.02% nicarbazin. Uniformly mix 0.8 – 1.6 pounds of Nicarb 25% with one of the feed ingredients to make at least 10 pounds of premix before final mixing. Mix the resulting premix with feed to make 1 ton (2000 lb) of finished feed containing 0.01 – 0.02% nicarbazin.

SUGGESTED DIRECTIONS FOR FEED TAGS

Use Directions

Use Nicarbazin Type C medicated feed as the only ration from the time chicks are placed on litter until past the time when coccidiosis is ordinarily a hazard.

CAUTION:

Do not feed to laying chickens.

Do not use as a treatment for outbreaks of coccidiosis. Do not use in flushing mashes.

If losses exceed 0.5 percent in a 2-day period, obtain an accurate diagnosis and follow the instructions of your veterinarian or poultry pathologist.

Broilers fed feed medicated with NICARB 25% may show reduced heat tolerance when exposed to high temperature and high humidity to which they have not been accustomed and under severe conditions, fatalities may result. An ample supply of drinking water and adequate ventilation will improve the birds’ tolerance of heat.

WARNING:

Withdraw 4 days before slaughter when used at levels ≤ 0.0125%.

Withdraw 5 days before slaughter when used at levels >0.0125%

Keep this and all drugs out of the reach of children.

NOT FOR HUMAN USE

RESTRICTED DRUG (CALIFORNIA) – USE ONLY AS DIRECTED

SEE DIRECTIONS ON BACK PANEL

Net Wt 50 lb (22.68 kg)

8205000

101-9018-13

Approved by FDA under NADA #009-476

NICARB REG TM Phibro Animal Health Corporation

MICROTRACER REG TM Micro-Tracers, Inc. San Francisco, CA

Generic Section

Distributed by:

Phibro Animal Health Corporation, Teaneck, NJ 07666

Nicarb 25 Label

Nicarb Label